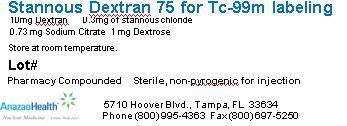 DRUG LABEL: Dextran 75
NDC: 51808-210 | Form: INJECTION, POWDER, LYOPHILIZED, FOR SOLUTION
Manufacturer: AnazaoHealth Corporation
Category: prescription | Type: HUMAN PRESCRIPTION DRUG LABEL
Date: 20120701

ACTIVE INGREDIENTS: DEXTRAN 75 10 mg/1 1
INACTIVE INGREDIENTS: STANNOUS CHLORIDE 0.3 mg/1 1; ANHYDROUS DEXTROSE 1 mg/1 1; SODIUM CITRATE 0.73 mg/1 1

Dextran 75

Dear Medical Professional,

Per your order, we have compounded Dextran 75 as a lyophilized powder for injection. The characteristics of this preparation are as follows:

DESCRIPTION

AnazaoHealth supplies compounded Dextran 75 for the preparation of Tc-99m Dextran 75. Each reaction vial contains 10 mg of Dextran 75, 0.30mg of stannous chloride, 0.73 mg Sodium Citrate and 1 mg of dextrose (lyophilized mixture, under nitrogen atmosphere), per unit dose vial.

Mechanism of Action

Dextran, when labeled with technetium Tc99m and given intravenously, is distributed throughout the body in much the same way as the patient’s serum, and serves as a suitable tracer with which to transiently image the vascular compartment

INDICATIONS AND USAGE

Technetium Tc99m Dextran by intravenous administration is indicated as a cardiac blood pool imaging agent and as an adjunct in the diagnosis of pericardial effusion, ventricular aneurysm, or GI Bleed

DOSAGE AND ADMINISTRATION

To prepare injection, up to 40 mCi of an oxidant-free sodium pertechnetate Tc 99m solution is aseptically injected into the vial, minimum volume 1ml, mix gently and let Dextran dissolve completely for 10 minutes

Storage and Handling

Injection should be administered within 6 hours after preparation. Before and after reconstitution- Store at room temperature

PACKAGE LABEL.PRINCIPAL DISPLAY PANEL

Figure 1